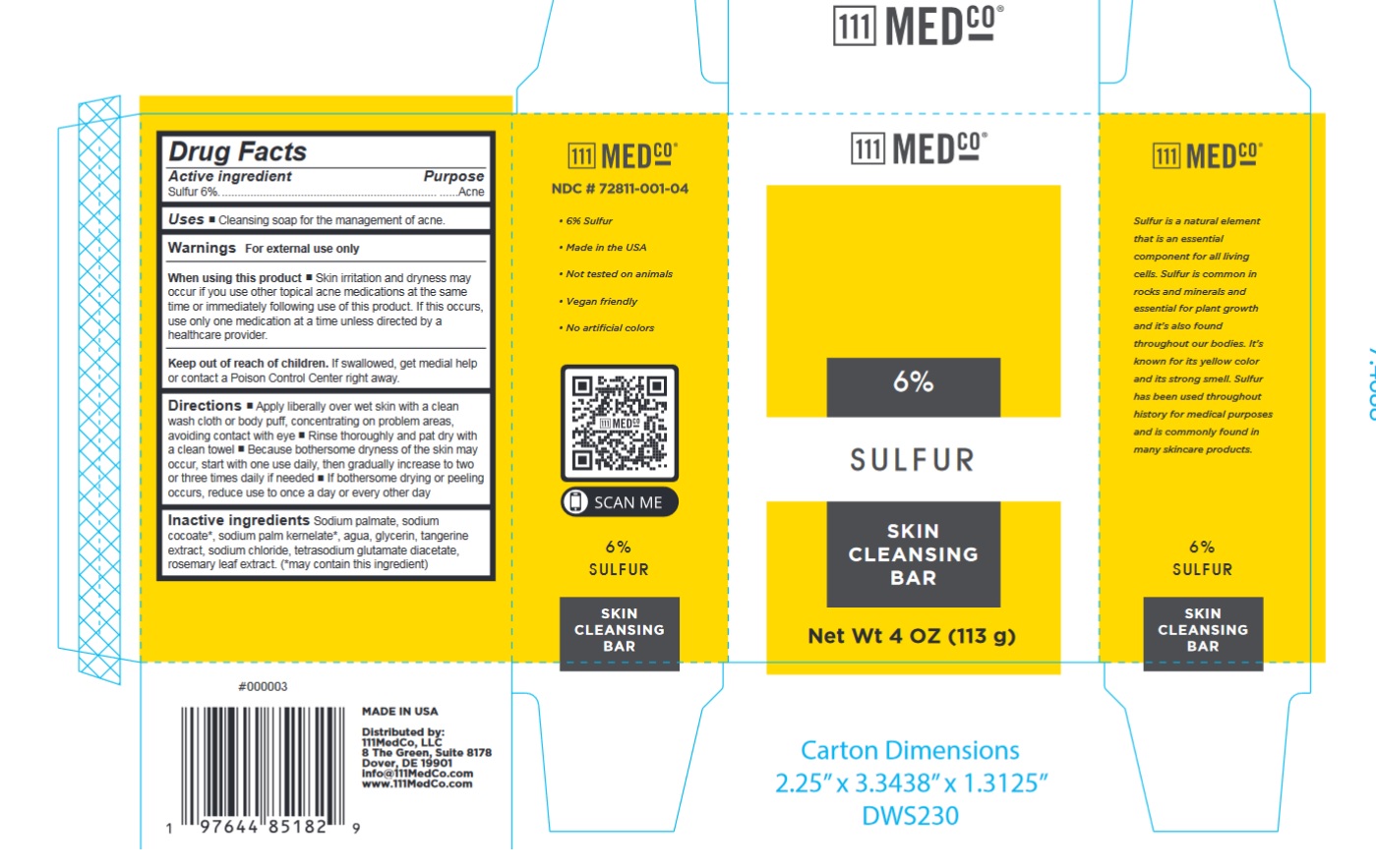 DRUG LABEL: 111MedCo 6% Sulfur Skin Cleansing Bar
NDC: 72811-001 | Form: SOAP
Manufacturer: 111MedCo LLC
Category: otc | Type: HUMAN OTC DRUG LABEL
Date: 20231212

ACTIVE INGREDIENTS: SULFUR 60 mg/1 g
INACTIVE INGREDIENTS: SODIUM PALMATE; SODIUM COCOATE; SODIUM PALM KERNELATE; WATER; GLYCERIN; TANGERINE; SODIUM CHLORIDE; TETRASODIUM GLUTAMATE DIACETATE; ROSEMARY

111MedCo 6% Sulfur Skin Cleansing Bar

Active ingredient

Sulfur 6%

Purpose

Acne

Uses

- Cleansing soap for the management of acne.

Warnings

For external use only

When using this product

Skin irritation and dryness may occur if you use other topical acne medications at the same time or immediately following use of this product. If this occurs, use only one medication at a time unless directed by a healthcare provider.

Keep out of reach of children.

If swallowed, get medial help or contact a Poison Control Center right away.

Directions

- Apply liberally over wet skin with a clean wash cloth or body puff, concentrating on problem areas, avoiding contact with eye
- Rinse thoroughly and pat dry with a clean towel
- Because bothersome dryness of the skin may occur, start with one use daily, then gradually increase to two or three times daily if needed
- If bothersome drying or peeling occurs, reduce use to once a day or every other day

Inactive ingredients

Sodium palmate, sodium cocoate*, sodium palm kernelate*, agua, glycerin, tangerine extract, sodium chloride, tetrasodium glutamate diacetate, rosemary leaf extract. (*may contain this ingredient)